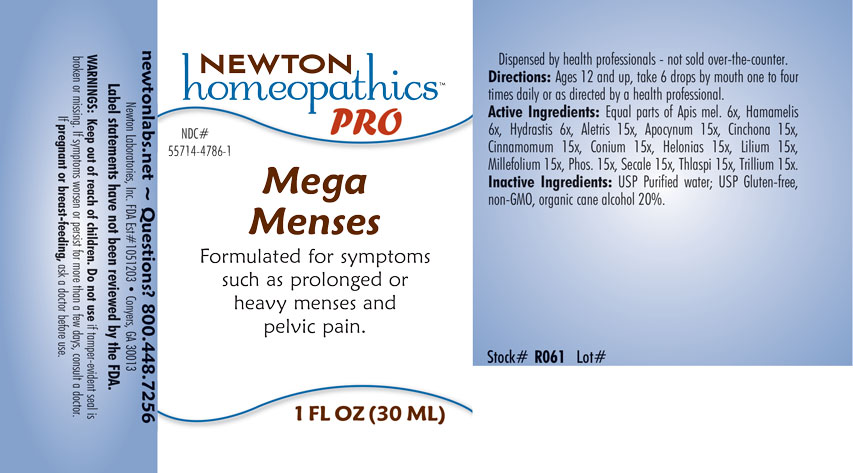 DRUG LABEL: Mega Menses
NDC: 55714-4786 | Form: LIQUID
Manufacturer: Newton Laboratories, Inc.
Category: homeopathic | Type: HUMAN OTC DRUG LABEL
Date: 20201204

ACTIVE INGREDIENTS: APIS MELLIFERA 6 [hp_X]/1 mL; CAPSELLA BURSA-PASTORIS 15 [hp_X]/1 mL; GOLDENSEAL 6 [hp_X]/1 mL; ALETRIS FARINOSA ROOT 15 [hp_X]/1 mL; APOCYNUM CANNABINUM ROOT 15 [hp_X]/1 mL; CINCHONA OFFICINALIS BARK 15 [hp_X]/1 mL; CINNAMON 15 [hp_X]/1 mL; CONIUM MACULATUM FLOWERING TOP 15 [hp_X]/1 mL; CHAMAELIRIUM LUTEUM ROOT 15 [hp_X]/1 mL; LILIUM LANCIFOLIUM WHOLE FLOWERING 15 [hp_X]/1 mL; ACHILLEA MILLEFOLIUM 15 [hp_X]/1 mL; PHOSPHORUS 15 [hp_X]/1 mL; CLAVICEPS PURPUREA SCLEROTIUM 15 [hp_X]/1 mL; HAMAMELIS VIRGINIANA ROOT BARK/STEM BARK 6 [hp_X]/1 mL; TRILLIUM ERECTUM ROOT 15 [hp_X]/1 mL
INACTIVE INGREDIENTS: WATER; ALCOHOL

Mega 4786L

INDICATIONS & USAGE SECTION

Formulated for symptoms such as prolonged or heavy menses and pelvic pain.

DOSAGE & ADMINISTRATION SECTION

Directions: Ages 12 and up take 6 drops by mouth one to four times daily or as directed by a health professional.

OTC - ACTIVE INGREDIENT SECTION

Equal parts of Apis mellifica 6x, Hamamelis virginiana 6x, Hydrastis canadensis 6x, Aletris farinosa 15x, Apocynum cannabinum 15x, Cinchona officinalis 15x, Cinnamomum 15x, Conium maculatum 15x, Helonias dioica 15x, Lilium tigrinum 15x, Millefolium 15x, Phosphorus 15x, Secale cornutum 15x, Thlaspi bursa-pastoris 15x, Trillium pendulum 15x.

OTC - PURPOSE SECTION

Formulated for symptoms such prolonged or heavy menses and pelvic pain.

INACTIVE INGREDIENT SECTION

Inactive Ingredients: USP Purified Water; USP Gluten-free, non-GMO, organic cane alcohol 20%.

QUESTIONS SECTION

newtonlabs.net - Questions? 800.448.7256

Newton Laboratories, Inc. FDA Est # 1051203 Conyers, GA 30013

WARNINGS SECTION

WARNINGS: Keep out of reach of children. Do not use if tamper-evident seal is broken or missing. If symptoms worsen or persist for more than a few days, consult a doctor. If pregnant or breast-feeding, ask a doctor before use.

OTC - PREGNANCY OR BREAST FEEDING SECTION

If pregnant or breast-feeding, ask a doctor before use.

OTC - KEEP OUT OF REACH OF CHILDREN SECTION

Keep out of reach of children.